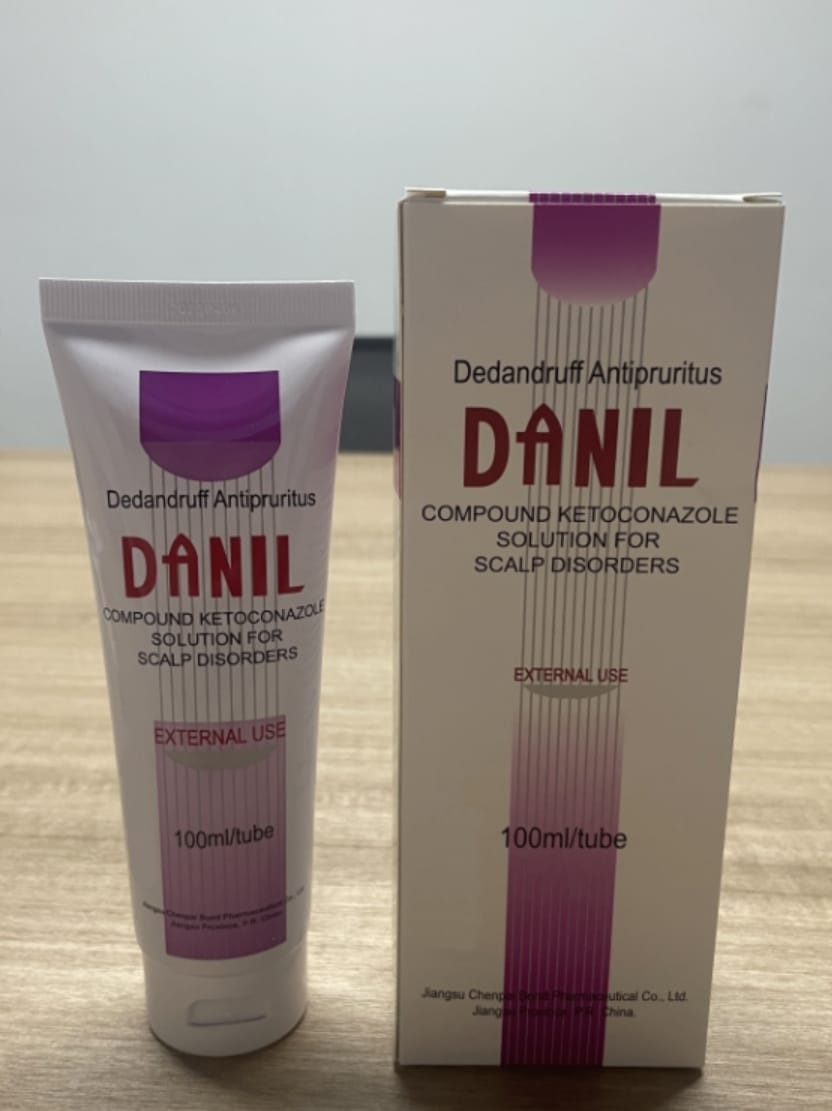 DRUG LABEL: Danil
NDC: 84277-5666 | Form: LOTION
Manufacturer: Jiangsu Chenpai Bond Pharmaceutical Co.,Ltd.
Category: otc | Type: HUMAN OTC DRUG LABEL
Date: 20250706

ACTIVE INGREDIENTS: KETOCONAZOLE 15 mg/1 g; CLOBETASOL PROPIONATE 0.25 mg/1 g
INACTIVE INGREDIENTS: CITRIC ACID ACETATE; EDETATE DISODIUM; COCONUT OIL GLYCERETH-8 ESTERS; PEG-14 1-((METHYLPHENYL)ETHYL)PHENYL ETHER AMMONIUM SULFATE; DIETHYLENE GLYCOL DISTEARATE; AA-1 CATION; MENTHOL; WATER; EOSIN B; GLYCEROL FORMAL; 2-(ETHYLSULFONYL)ETHANOL; SODIUM LAURYL SULFATE

DOSAGE AND ADMINISTRATION: External use only. Apply about 5ml of DANIL solution to moist hair, massage it gently to let the solution contact with the scalp thoroughly, after 3~5 minutes, rinse cleanly with water. For treatment purpose , the DANIL solution should be used twice/thrice a week continuously for 2~4 weeks; for prevention purpose, it should be used once every one or two weeks.

WARNINGS

There is no any special warning.

INACTIVE INGREDIENT

Clobetasol propionate 0.25mg

INDICATIONS AND USAGE

EXPIRATION DATE: Three years after the manufactured date. For external use only. Avoid contact with eyes. Keep out of reach of children. Do not exceed prescribed dose. Read package insert carefully before using.

KEEP OUT OF REACH OF CHILDREN

PRECAUTIONS: 1. Avoid contact with the eyes and other mucous membranes(oral and nasal). 2. Stop and clean the drug, if burning sensation and red swelling of the skin appears. Consult with the doctor, if necessary. 3. Consult with the doctor or pharmacist if it is necessary to use DANIL for more than 4 weeks continuously. 4. You can use other hair-care product if your hair is dry after using DANIL. 5. Infants and children should use it with cautions. 6. It is contraindicated for individuals who have known or suspected hypersensitivity to any of its ingredients. It should be used with cautions in individuals with allergic constitution. 7. Do not use it if the appearance of the solution is changed. 8. Keep it out of the reach of children. 9. Children should use it under the supervision of adults. 10. Consult a doctor or pharmacist before use DANIL, if you are using any other medicines at the same time.

PURPOSE

PHARMACOLOGICAL ACTION: In vitro, DANIL solution exhibits a potent antimycotic activity. In vivo studies in animal patterns infected with superficial fungi, it is shown that DANIL solution has an excellent therapeutic effect, especially for that caused by Pityrosporum oval. Combined with Clobetasol propionate, a potent anti-inflammatory and anti-pruritic topical corticosteroid agent, DANIL solution has the actions of anti-bacterial, anti-inflammatory, anti-allergic, anti-dandruff and anti-pruritus. Clinical trial reports that the DANIL solution has proved to be more effective and more rapid in treatment of dandruff and seborrheic dermatitis on the scalp than the single Ketoconazole lotion. Animal acute toxicity test and toxicity test for local application and clinical trial indicated that the DANIL solution is safe for use, no allergic or irritant reaction is found.

Active Ingredients:

Ketoconazole 15mg
Clobetasol Propionate 0.25mg

PACKAGE LABEL

COMPOUND KETOCONAZOLE SOLUTION FOR SCALP DISORDERS